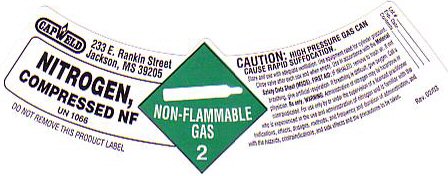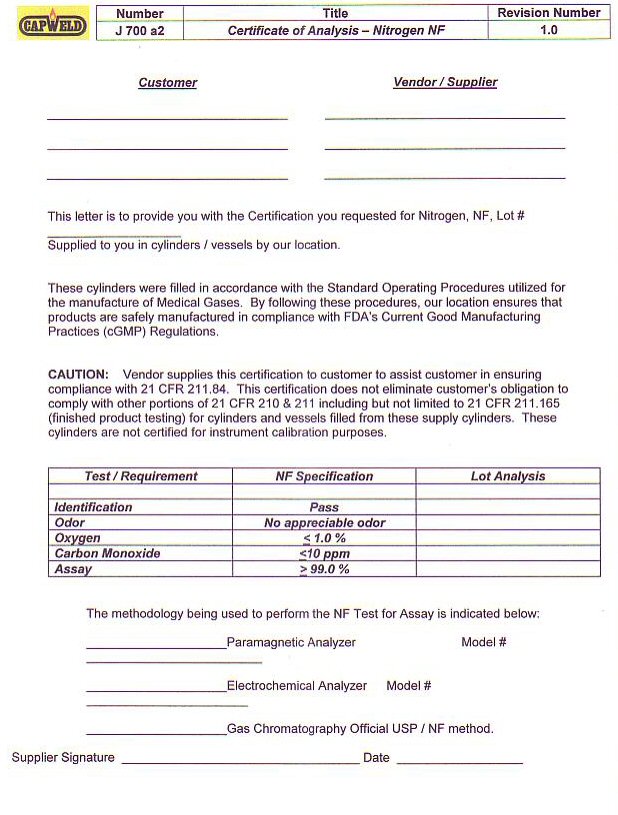 DRUG LABEL: NITROGEN
NDC: 52849-200 | Form: GAS
Manufacturer: Capweld Inc
Category: prescription | Type: HUMAN PRESCRIPTION DRUG LABEL
Date: 20100101

ACTIVE INGREDIENTS: NITROGEN 99 L/100 L

NITROGEN COMPRESSED LABEL

NITROGEN COMPRESSED NF UN 1066
CAUTION; HIGH PRESSURE GAS CAN CAUSE RAPID SUFFOCATION Store and use with adequate ventilation use equipment rated for cylinder pressure Close valve when not in use and when empty. Use in accordance with suppliers Material Safety Data Sheet.
FIRST AID: If inhaled, remove to fresh air. If not breathing, give
artificial respiration. If breathing is difficult, give oxygen. Call
a physician.
Do Not Remove this Product Label

NITROGEN CERTIFICATE OF ANALYSIS

CUSTOMER ___________________ VENDOR / SUPPLIER ________________________ THIS LETTER IS TO PROVIDE YOU WITH THE
CERTIFICATION YOU REQUESTED FOR OXYGEN USP LOT NUMBER _______________________ SUPPLIED TO YOU IN
CYLINDERS / VESSELS BY OUR LOCATION
These cylinders were filled in accordance with the Standard Operating
Procedures utilized for the manufacture of Medical Gases. By
following these procedures, our location ensures that products are
safely manufactured in compliance with FDA’s Current Good Manufacturing
Practices
(cGMP) Regulations.
CAUTION: VENDOR SUPPLIES THIS CERTIFICATION TO CUSTOMER TO ASSIST
CUSTOMER IN ENSURING COMPLIANCE WITH 21 CFR 211.84. THIS
CERTIFICATION DOES NOT ELIMINATE CUSTOMERS OBLIGATION TO COMPLY WITH
OTHER PORTIONS OF 21 CFR 210 AND 211, INCLUDING BUT NOT
LIMITED TO 21 CFR 211.165 (FINISHED PRODUCT TESTING) FOR CYLINDERS AND
VESSELS FILLED FROM THESE SUPPLY CYLINDERS. THESE CYLINDERS ARE
NOT CERTIFIED FOR INSTRUMENT CALIBRATION.
TEST REQUIREMENT NF SPECIFICATION LOT ANALYSIS
IDENTIFICATION PASS
ODOR PASS
Oxygen LESS THAT 1.0%
CARBON MONOXIDE LESS THAT 0.001%
ASSAY GREATER THAN 99.0%
The methodology being used to perform the USP / NF Test for
Assay is indicated below: Paramagnetic Analyzer Model # _________________________
Electrochemical Analyzer Model # _________________________
Gas Chromatography Official USP/NF method
Supplier Signature ____________________________ Date _______________________
J 700 a2

GENERAL WARNINGS AND PRECAUTIONS

WARNING: Administration of nitrogen may be hazardous or contraindicated. For
use only by or under the supervision of a licensed practitioner who is
experienced in the use and administration of nitrogen and is familiar
with the indications, effects, dosages, methods, and frequency and
duration of administration and with hazards, contraindications, and
side effects and the precautions to be taken. Rx Only